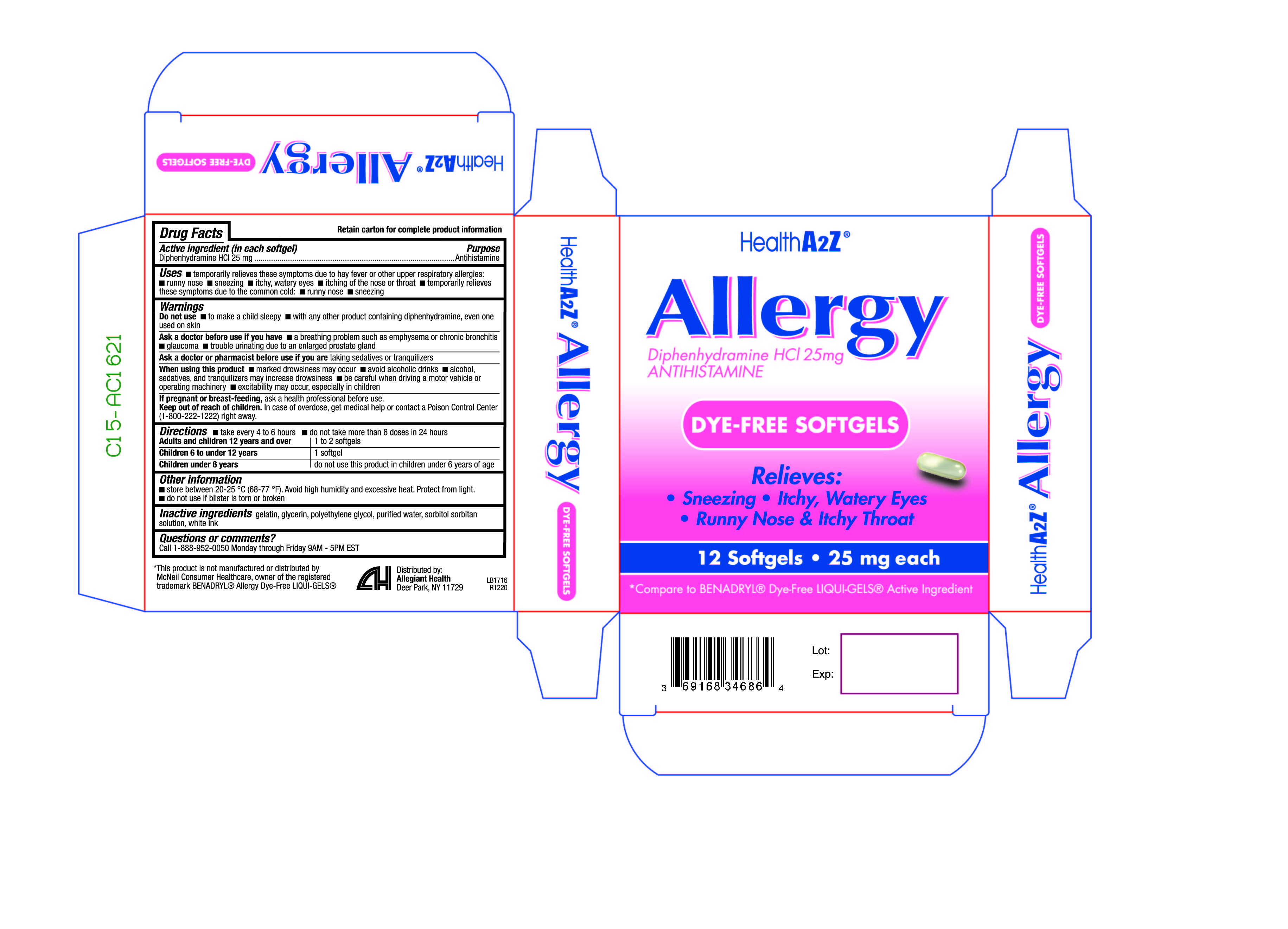 DRUG LABEL: Allergy DyeFree
NDC: 69168-409 | Form: CAPSULE, LIQUID FILLED
Manufacturer: Allegiant Health
Category: otc | Type: HUMAN OTC DRUG LABEL
Date: 20210426

ACTIVE INGREDIENTS: DIPHENHYDRAMINE HYDROCHLORIDE 25 mg/1 1
INACTIVE INGREDIENTS: GELATIN; GLYCERIN; POLYETHYLENE GLYCOL, UNSPECIFIED; WATER; SORBITOL SOLUTION

409 - Allergy Dye Free

Active ingredient(s)

Diphenhydramine HCl 25 mg

Purpose

Antihistamine

Use(s)

temporarily relieves these symptoms due to hay fever or other upper respiratory allergies:

- runny nose
- sneezing
- itchy, watery eyes
- itching of the nose or throat

temporarily relieves these symptoms due to the common cold:

- runny nose
- sneezing

Warnings

Do not use

- to make a child sleepy
- with any other product containing diphenhydramine, even one used on skin

Ask a doctor before use if

- a breathing problem such as emphysema or chronic bronchitis
- glaucoma
- trouble urinating due to an enlarged prostate gland

Ask a doctor or pharmacist before use if

taking sedatives or tranquilizers

When using this product

- marked drowsiness may occur
- avoid alcoholic drinks
- alcohol, sedatives, and tranquilizers may increase drowsiness
- be careful when driving a motor vehicle or operating machinery
- excitability may occur, especially in children

Pregnancy/Breastfeeding

ask a health professional before use.

Keep out of reach of children

In case of overdose, get medical help or contact a Poison Control Center (1-800-222-1222) right away.

Directions

- take every 4 to 6 hours
- do not take more than 6 doses in 24 hours

Adults and children 12 years and over: 1 to 2 softgels

Children 6 to under 12 years: 1 softgel

Children under 6 years: do not use this product in children under 6 years of age

Other information

- do not use if blister is torn or broken

Storage

- store between 20-25 °C (68-77 °F).
- Avoid high humidity and excessive heat. Protect from light.

Inactive ingredients

gelatin, glycerin, polyethylene glycol, purified water, sorbitol sorbitan solution, white ink

Questions

Call 1-888-952-0050
Monday through Friday 9AM - 5PM EST

Principal Display Panel

Diphenhydramine HCL 25mg